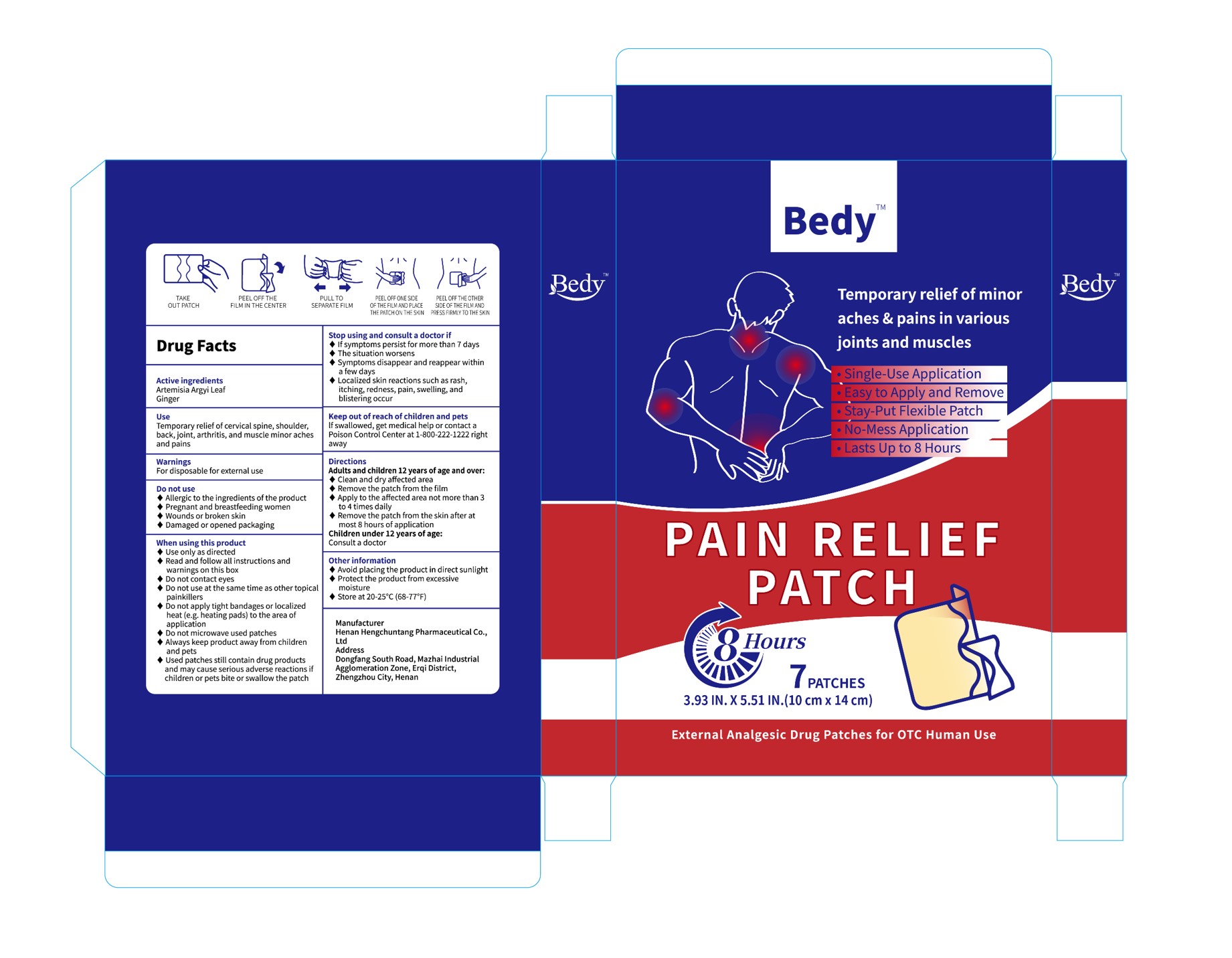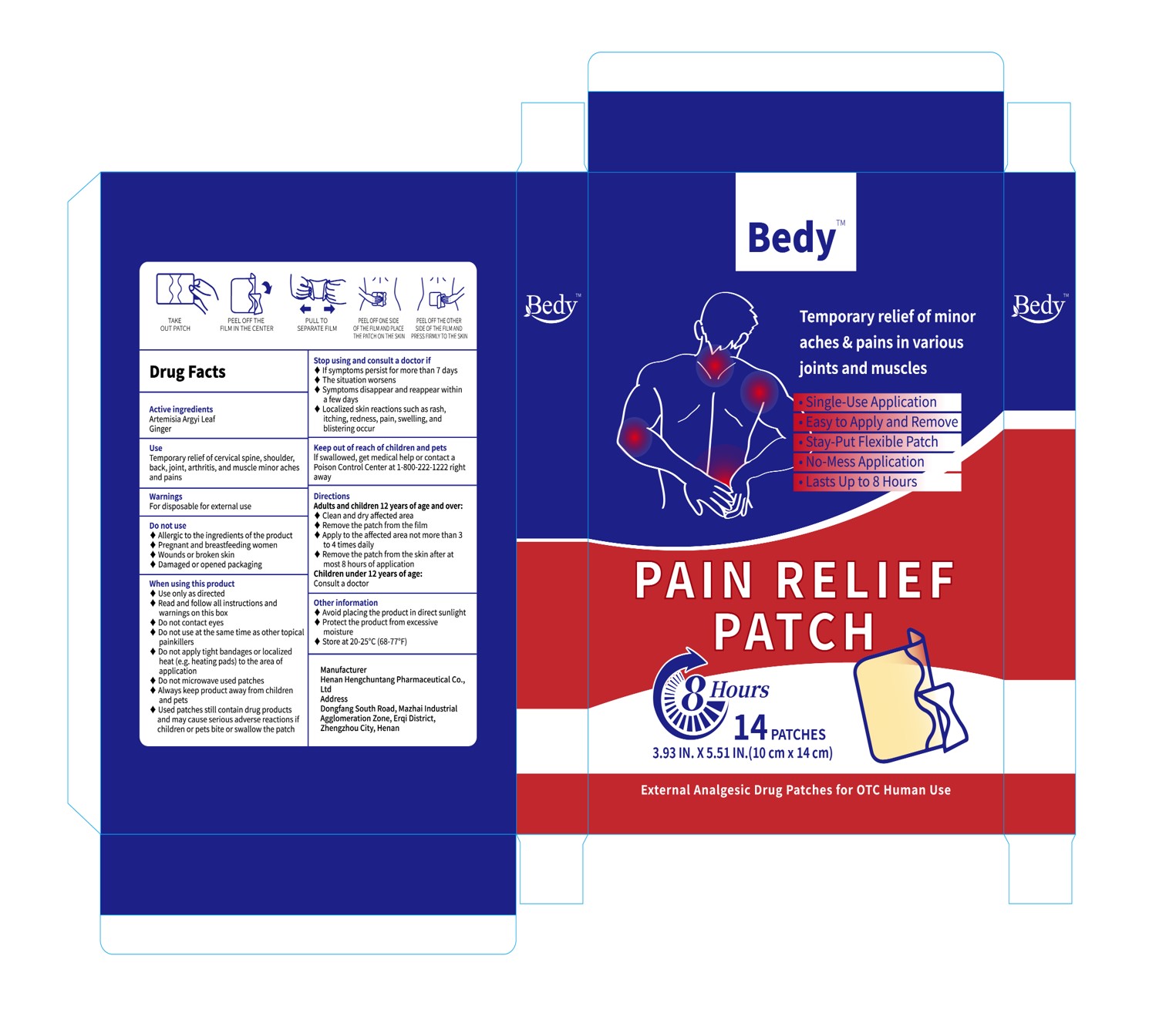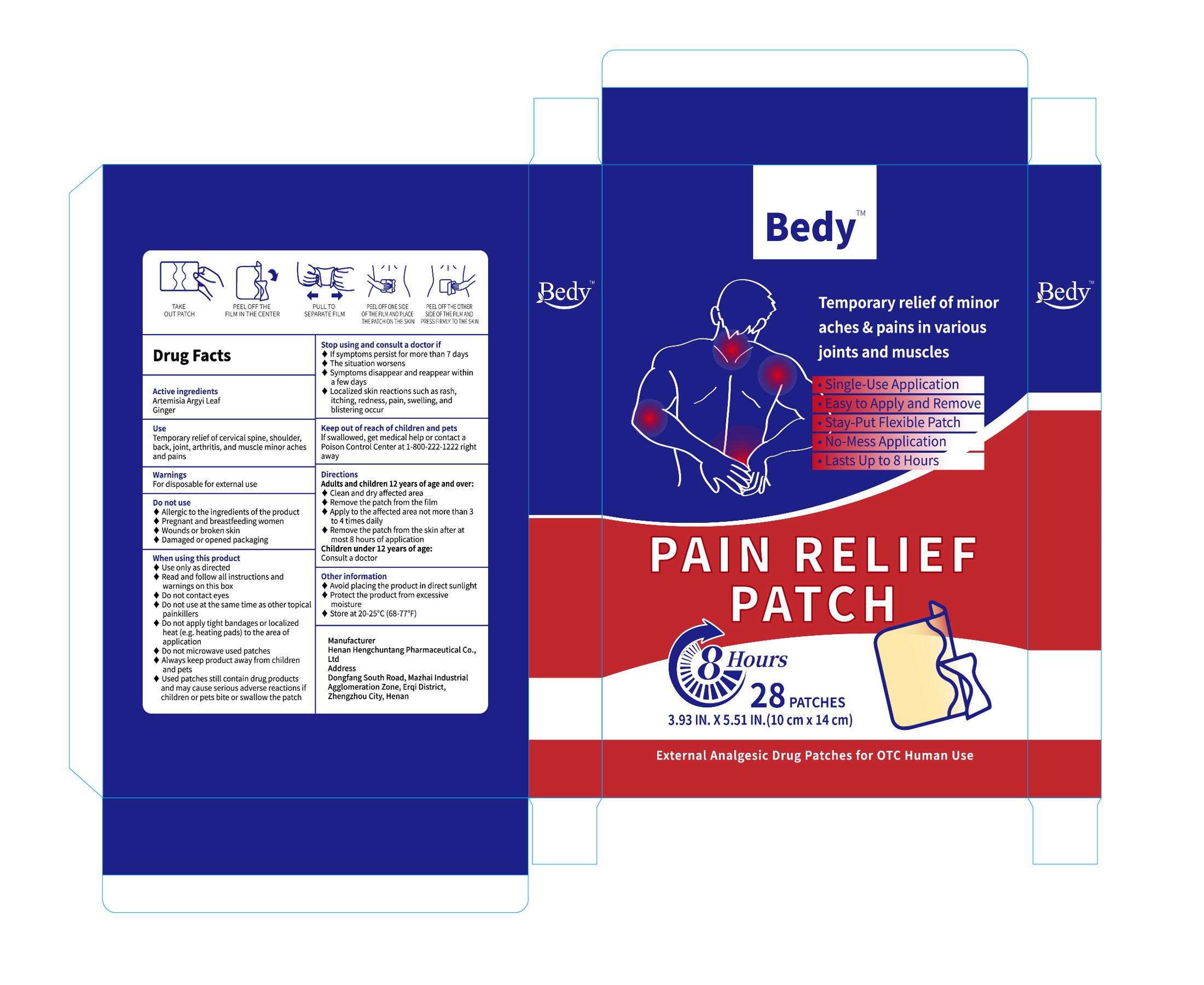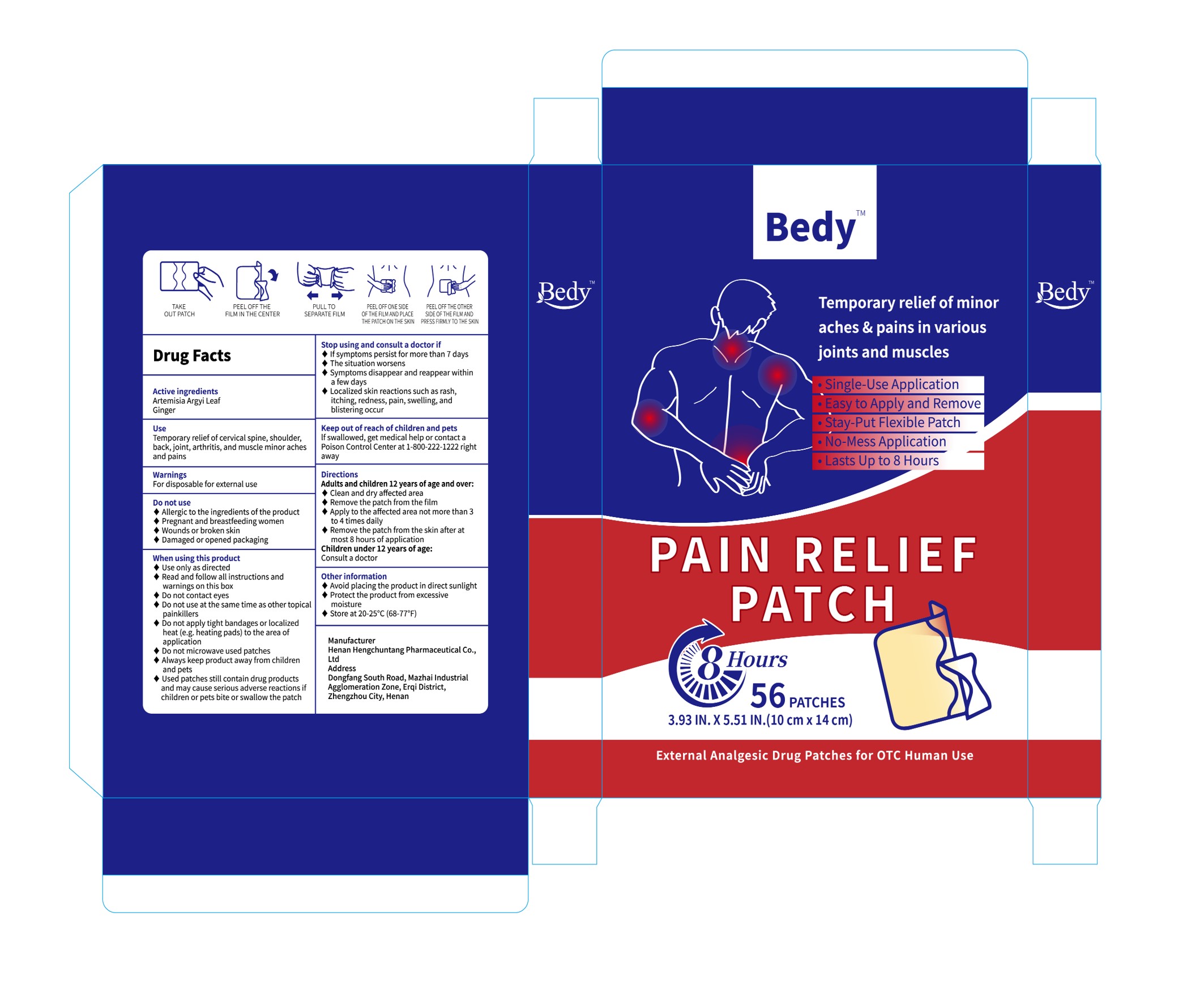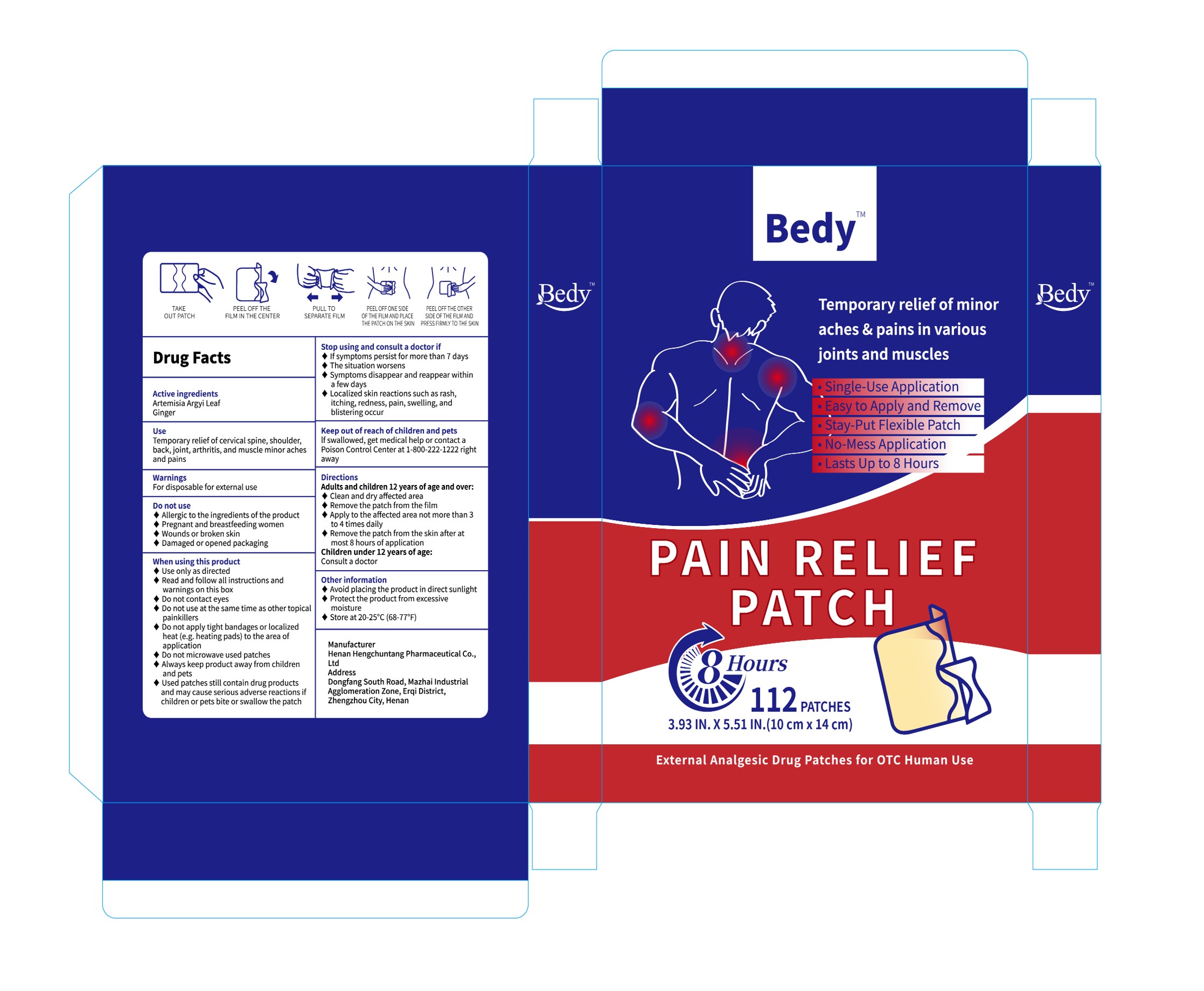 DRUG LABEL: Bedy Pain Relief
NDC: 85152-004 | Form: PATCH
Manufacturer: Henan Hengchuntang Pharmaceutical Co., Ltd
Category: otc | Type: HUMAN OTC DRUG LABEL
Date: 20250222

ACTIVE INGREDIENTS: ARTEMISIA ARGYI LEAF 1 g/100 g; GINGER 2 g/100 g
INACTIVE INGREDIENTS: ETHYLENE-VINYL ACETATE COPOLYMER (28% VINYL ACETATE); COTTON

Active Ingredient

ARTEMISIA ARGYI LEAF
GINGER

Inactive ingredient

EVA-28
COTTON

Purpose

Temporary relief of cervical spine, shoulder,back, joint, arthritis, and muscle minor achesand pains

When using

When using this product

Use only as directedRead and follow all instructions andwarnings on this boxDo not contact eyesDo not use at the same time as other topicalpainkillers
Do not apply tight bandages or localizedheat (e.g. heating pads) to the area ofapplication
Do not microwave used patchesAlways keep product away from children and pets

Used patches still contain drug productsand may cause serious adverse reactions ifchildren or pets bite or swallow the patch

Do not use

Allergic to the ingredients of the product

Pregnant and breastfeeding women

Wounds or broken skin

Damaged or opened packaging

keep it out of reach of children

keep product away from childrenand pets

Dosage

Clean and dry affected areaRemove the patch from the filmApply to the affected area not more than 3to 4 times dailyRemove the patch from the skin after atmost 8 hours of application

Warnings

WarningsFor disposable for external use

Indication

DirectionsAdults and children 12 years of age and over:◆Clean and dry affected areaRemove the patch from the filmApply to the affected area not more than 3to 4 times dailyRemove the patch from the skin after atmost 8 hours of applicationChildren under 12 years of age:Consult a doctor